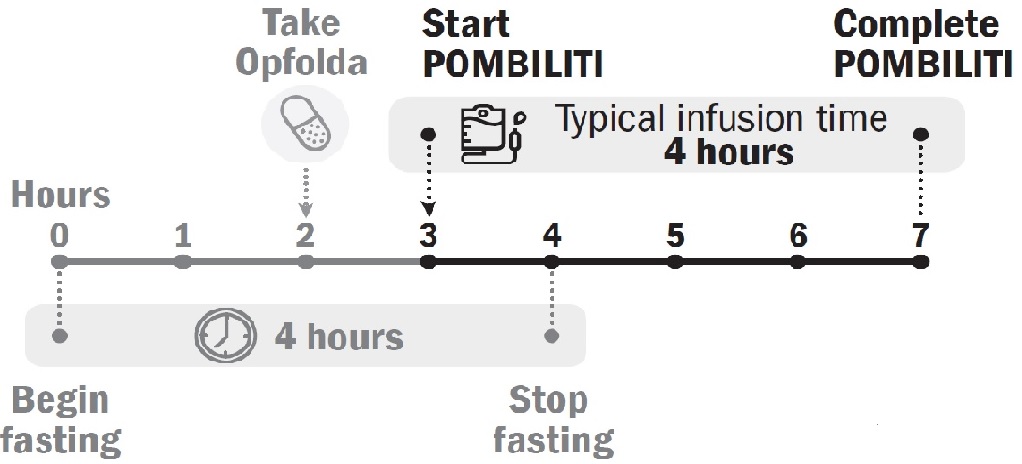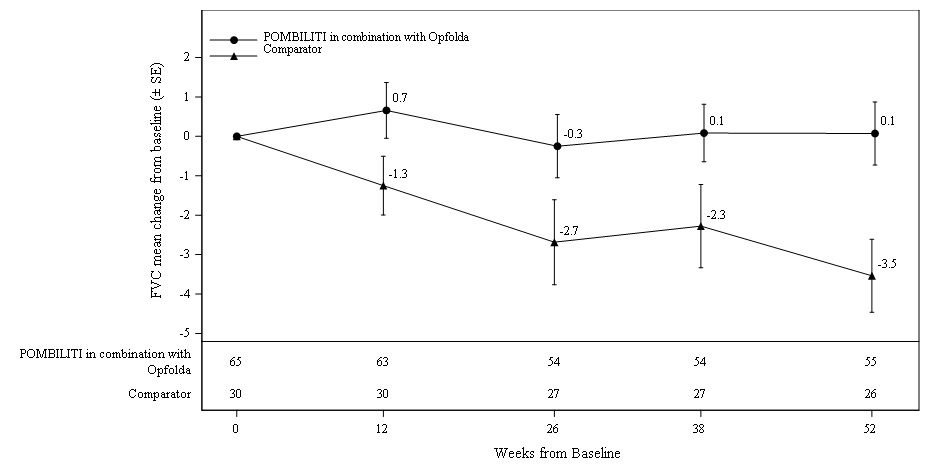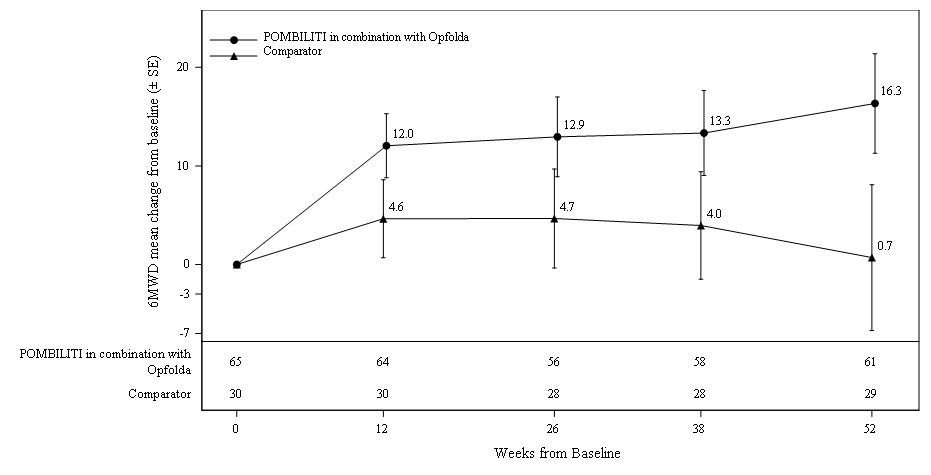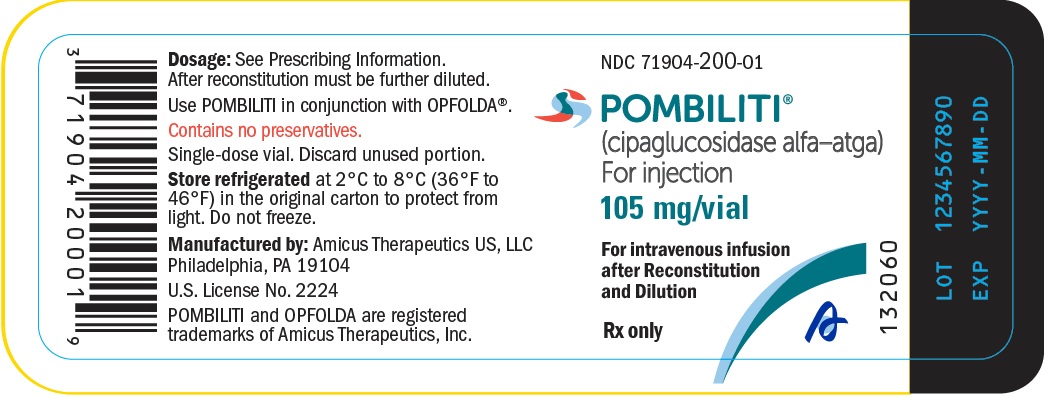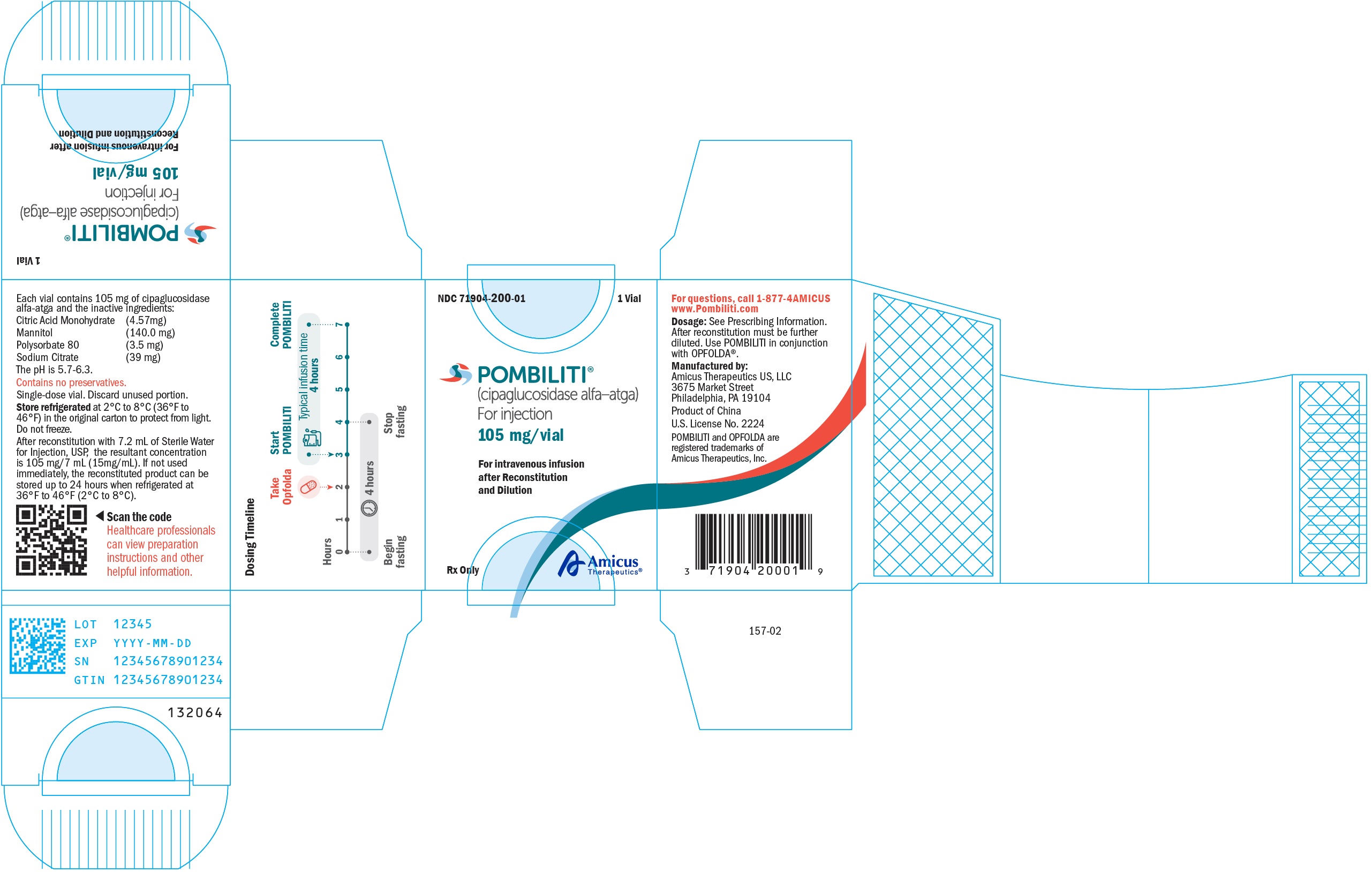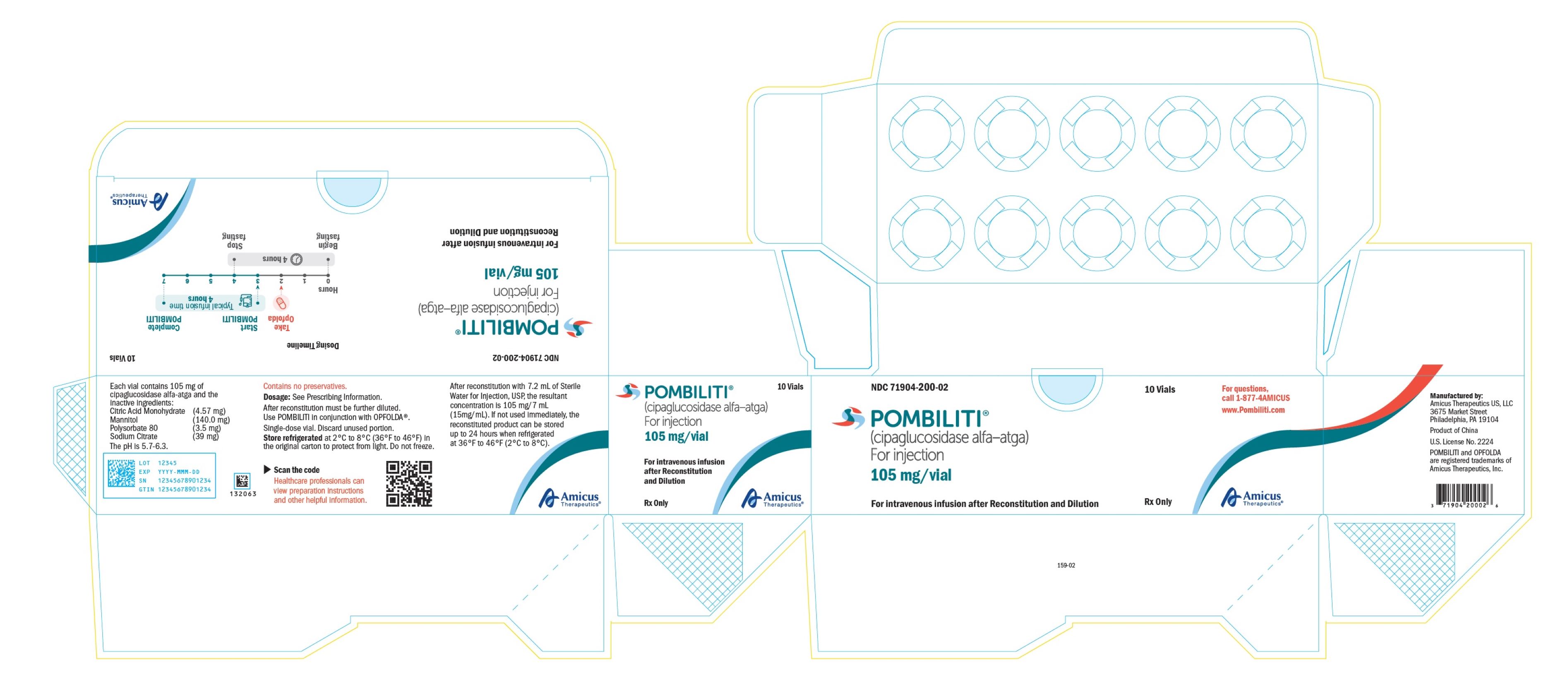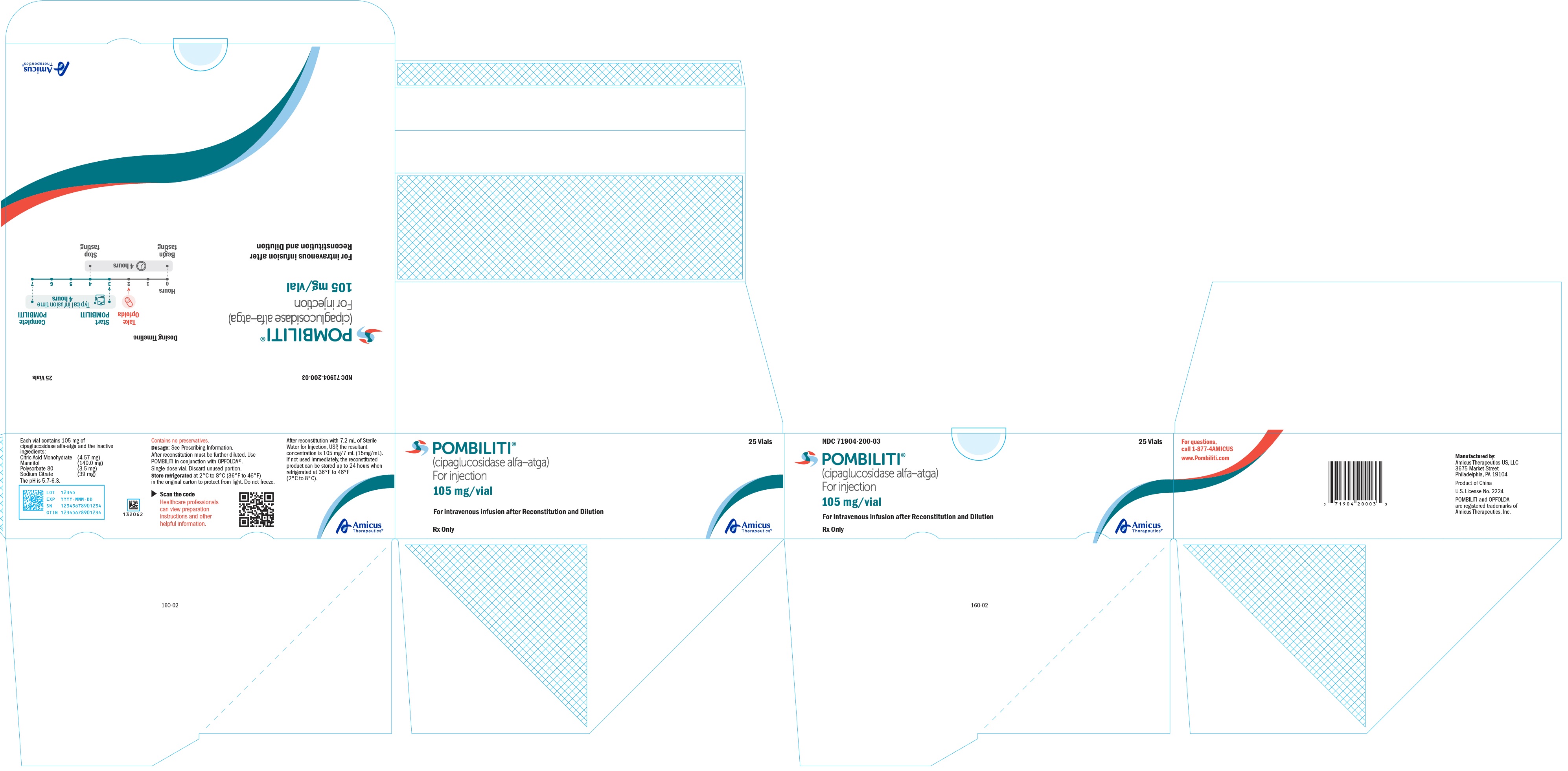 DRUG LABEL: POMBILITI
NDC: 71904-200 | Form: INJECTION, POWDER, LYOPHILIZED, FOR SOLUTION
Manufacturer: AMICUS THERAPEUTICS US, LLC
Category: prescription | Type: HUMAN PRESCRIPTION DRUG LABEL
Date: 20241127

ACTIVE INGREDIENTS: CIPAGLUCOSIDASE ALFA 105 mg/1 1

HIGHLIGHTS OF PRESCRIBING INFORMATION

These highlights do not include all the information needed to use POMBILITI® safely and effectively. See full prescribing information for POMBILITI.
POMBILITI (cipaglucosidase alfa-atga) for injection, for intravenous use
Initial U.S. Approval: 2023

WARNING: SEVERE HYPERSENSITIVITY REACTIONS, INFUSION-ASSOCIATED REACTIONS, and RISK OF ACUTE CARDIORESPIRATORY FAILURE IN SUSCEPTIBLE PATIENTS

See full prescribing information for complete boxed warning

- Hypersensitivity Reactions Including Anaphylaxis
  Appropriate medical support measures, including cardiopulmonary resuscitation equipment, should be readily available. If a severe hypersensitivity reaction occurs, POMBILITI should be discontinued immediately and appropriate medical treatment should be initiated. (5.1)
- Infusion-Associated Reactions (IARs)
  If severe IARs occur, immediately discontinue POMBILITI and initiate appropriate medical treatment. (5.2)
- Risk of Acute Cardiorespiratory Failure in Susceptible Patients
  Patients susceptible to fluid volume overload, or those with acute underlying respiratory illness or compromised cardiac or respiratory function, may be at risk of serious exacerbation of their cardiac or respiratory status during POMBILITI infusion. (5.3)

1 INDICATIONS AND USAGE

POMBILITI is a hydrolytic lysosomal glycogen-specific enzyme indicated, in combination with Opfolda, an enzyme stabilizer, for the treatment of adult patients with late-onset Pompe disease (lysosomal acid alpha-glucosidase [GAA] deficiency) weighing ≥40 kg and who are not improving on their current enzyme replacement therapy (ERT). (1)

2 DOSAGE AND ADMINISTRATION

- Verify pregnancy status in females of reproductive potential prior to initiating treatment. (2.1)
- Administer POMBILITI in combination with Opfolda. (2.2)
- Consider administering antihistamines, antipyretics, and/or corticosteroids prior to POMBILITI administration. (2.2)
- Recommended POMBILITI dosage is 20 mg/kg (of actual body weight) administered every other week as an intravenous infusion over approximately 4 hours. (2.2)
- Start POMBILITI in combination with Opfolda 2 weeks after the last ERT dose. (2.2)
- Initiate the POMBILITI infusion approximately 1 hour after oral administration of Opfolda. If the POMBILITI infusion cannot be started within 3 hours of oral administration of Opfolda, reschedule POMBILITI in combination with Opfolda at least 24 hours after Opfolda was last taken. If POMBILITI in combination with Opfolda are both missed, re-start treatment as soon as possible. (2.2)
- See the full prescribing information for dosage modifications due to hypersensitivity reactions or IARs. (2.3)
- Must be reconstituted and diluted prior to use. (2.4)
- See the full prescribing information for administration instructions. (2.6)

3 DOSAGE FORMS AND STRENGTHS

For injection: 105 mg of cipaglucosidase alfa-atga as a lyophilized powder in a single-dose vial for reconstitution. (3)

4 CONTRAINDICATIONS

Pregnancy (4, 5.4, 8.1)

5 WARNINGS AND PRECAUTIONS

- Embryo-Fetal Toxicity: May cause embryo-fetal harm. Advise females of reproductive potential of the potential risk to a fetus and to use effective contraception during treatment and for at least 60 days after the last dose. (4, 5.4, 8.1, 8.3)
- Risks Associated with Opfolda: Refer to the Opfolda Prescribing Information for a description of additional risks for Opfolda. (5.5)

6 ADVERSE REACTIONS

Most common adverse reactions ≥ 5% are headache, diarrhea, fatigue, nausea, abdominal pain and pyrexia. (6.1)

To report SUSPECTED ADVERSE REACTIONS, contact Amicus Therapeutics at 1-877-4AMICUS or FDA at 1-800-FDA-1088 or www.fda.gov/medwatch.

8 USE IN SPECIFIC POPULATIONS

Lactation: Breastfeeding not recommended. (8.2)

FULL PRESCRIBING INFORMATION

WARNING: SEVERE HYPERSENSITIVITY REACTIONS, INFUSION-ASSOCIATED REACTIONS, and RISK OF ACUTE CARDIORESPIRATORY FAILURE IN SUSCEPTIBLE PATIENTS

Hypersensitivity Reactions Including Anaphylaxis
Patients treated with POMBILITI have experienced life-threatening hypersensitivity reactions, including anaphylaxis. Appropriate medical support measures, including cardiopulmonary resuscitation equipment, should be readily available during POMBILITI administration. If a severe hypersensitivity reaction (e.g., anaphylaxis) occurs, POMBILITI should be discontinued immediately, and appropriate medical treatment should be initiated. In patients with severe hypersensitivity reaction, desensitization measures to POMBILITI may be considered [see Warnings and Precautions (5.1)].

Infusion-Associated Reactions (IARs)
Patients treated with POMBILITI have experienced severe IARs. If severe IARs occur, immediately discontinue the POMBILITI infusion, initiate appropriate medical treatment, and assess the benefits and risks of readministering POMBILITI following severe IARs. Patients with an acute underlying illness at the time of POMBILITI infusion may be at greater risk for IARs. Patients with advanced Pompe disease may have compromised cardiac and respiratory function, which may predispose them to a higher risk of severe complications from IARs [see Warnings and Precautions (5.2)].

Risk of Acute Cardiorespiratory Failure in Susceptible Patients
Patients susceptible to fluid volume overload, or those with acute underlying respiratory illness or compromised cardiac or respiratory function for whom fluid restriction is indicated may be at risk of serious exacerbation of their cardiac or respiratory status during POMBILITI infusion. More frequent monitoring of vitals should be performed during POMBILITI infusion in such patients [see Warnings and Precautions (5.3)].

1 INDICATIONS AND USAGE

POMBILITI is indicated, in combination with Opfolda, for the treatment of adult patients with late-onset Pompe disease (lysosomal acid alpha-glucosidase [GAA] deficiency) weighing ≥40 kg and who are not improving on their current enzyme replacement therapy (ERT).

2 DOSAGE AND ADMINISTRATION

2.1 Pregnancy Evaluation Prior to Initiating Treatment

Verify the pregnancy status of females of reproductive potential prior to initiating POMBILITI in combination with Opfolda [see Use in Specific Populations (8.1, 8.3)].

2.2 Recommended Dosage and Administration

POMBILITI must be administered in combination with Opfolda (see Figure 1 for the dosing timeline). If the Opfolda dose is missed, POMBILITI should not be administered. Refer to the Opfolda Prescribing Information for Opfolda dosage and administration recommendations.

Prior to POMBILITI administration, consider pretreating with antihistamines, antipyretics, and/or corticosteroids [see Warnings and Precautions (5.1, 5.2)]. If premedication was used with previous enzyme replacement therapy (ERT), prior to POMBILITI administration, pretreat with antihistamines, antipyretics, and/or corticosteroids.

The recommended dosage of POMBILITI is 20 mg/kg (of actual body weight) administered every other week as an intravenous infusion over approximately 4 hours (see Table 1 for the recommended total infusion volume based on the patient’s weight).

Start POMBILITI in combination with Opfolda 2 weeks after the last ERT dose.

Initiate the POMBILITI infusion approximately 1 hour after oral administration of Opfolda. If the POMBILITI infusion cannot be started within 3 hours of oral administration of Opfolda, reschedule POMBILITI in combination with Opfolda at least 24 hours after Opfolda was last taken. If POMBILITI in combination with Opfolda are both missed, re-start treatment as soon as possible.

Figure 1. Dosing Timeline

2.3 Dosage and Administration Modifications Due to Hypersensitivity Reactions and/or Infusion-Associated Reactions

In the event of a severe hypersensitivity reaction (including anaphylaxis) or a severe infusion-associated reaction (IAR), immediately discontinue the POMBILITI infusion, and initiate appropriate medical treatment. For additional recommendations in the event of a severe hypersensitivity reaction [see Warnings and Precautions (5.1, 5.2)].

In the event of a mild to moderate hypersensitivity reaction or moderate IAR, consider temporarily holding or slowing the infusion rate and initiating appropriate medical treatment [see Warnings and Precautions (5.1, 5.2)]. If symptoms:

- Persist despite temporarily holding or slowing the infusion, stop the infusion for 30 to 60 minutes, monitor the patient, and consider resuming the infusion at a reduced rate if symptoms have improved. If symptoms continue to persist, discontinue the infusion, and consider re-initiating the infusion within 7 to 14 days with appropriate premedication.
- Subside following holding or slowing the infusion, increase the infusion rate to the rate at which the reaction occurred and consider continuing to increase the rate (every 30 minutes) in a stepwise manner up to the target infusion rate. Closely monitor the patient.

2.4 Reconstitution and Dilution Instructions

Use aseptic technique during preparation. Reconstitute and dilute POMBILITI in the following manner:

Reconstitute the Lyophilized Powder

- Determine the number of POMBILITI vials to be reconstituted based on the calculated dose (based on patient’s actual body weight in kg) [see (Dosage and Administration 2.2)].
- Remove vials from the refrigerator and set aside for approximately 30 minutes to allow vials to come to room temperature.
- Reconstitute each vial by slowly injecting 7.2 mL of Sterile Water for Injection, down the inside wall of each vial to avoid foaming. Avoid forceful impact of Sterile Water for Injection on the lyophilized powder and avoid foaming.
- Roll and tilt each vial to allow the lyophilized powder to dissolve completely which typically takes 2 minutes. Each vial will yield a concentration of 15 mg/mL. Do not invert, swirl, or shake.
- Visually inspect the reconstituted solution for particulate matter and discoloration. The reconstituted solution appears as a clear to opalescent, colorless to yellowish solution essentially particle free. Discard if foreign matter is observed or the solution is discolored.

Dilute the Reconstituted Solution

- Remove airspace within a bag of 0.9% Sodium Chloride Injection. Remove an equal volume of 0.9% Sodium Chloride Injection from the bag that will be replaced by the total volume (mL) of reconstituted POMBILITI (see Table 1 for the recommended total infusion volume based on the patient’s weight).
- Slowly withdraw 7 mL of reconstituted solution from each of the vials until the patient’s dose is obtained. Discard any remaining reconstituted solution in the last vial.
- Add the reconstituted solution slowly and directly into the infusion bag.
- To prevent foaming, gently invert infusion bag to mix the solution and avoid vigorous shaking or agitation. After dilution, the solution will have a final concentration of 0.5 to 4 mg/mL of cipaglucosidase alfa-atga. Do not use a pneumatic tube to transport the infusion bag.
- Administer the diluted solution at room temperature without delay [see (Dosage and Administration 2.6)].

2.5 Storage Instructions for the Reconstituted and Diluted Product

Storage of the Reconstituted Solution
If the reconstituted POMBILITI vials are not used immediately, store refrigerated at 2°C to 8°C (36°F to 46°F) for up to 24 hours. Do not freeze.

Storage of the Diluted Solution
If the diluted solution is not administered immediately, store refrigerated at 2°C to 8°C (36°F to 46°F) for up to 16 hours. Storage at room temperature is not recommended. Do not freeze.

After removal of the diluted solution from the refrigerator:

- Completely infuse within 6 hours.
- Do not restore in the refrigerator.

Discard the diluted solution if refrigerated more than 16 hours or if the diluted solution is not able to be completely infused within 6 hours after removal from the refrigerator.

2.6 Administration Instructions

Prior to administration, inspect the infusion bag for foaming. If foaming is present, let foam dissipate before administering POMBILITI. If the diluted solution has been refrigerated, allow solution to equilibrate to room temperature for 30 minutes prior to infusion.

Use an administration set with an inline low protein binding 0.2‑micron filter to administer POMBILITI. Change filter if the filter becomes blocked.

Initiate the POMBILITI infusion approximately 1 hour after oral administration of Opfolda. In the event of POMBILITI infusion delay, the starting infusion time should not exceed 3 hours from the oral administration of Opfolda [see (Dosage and Administration 2.2)].

The initial recommended infusion rate is 1 mg/kg/hour (see Table 1). Gradually increase the infusion rate by 2 mg/kg/hour every 30 minutes if there are no signs of hypersensitivity or infusion-associated reactions (IARs) until a maximum rate of 7 mg/kg/hour is reached; then, maintain the infusion rate at 7 mg/kg/hour until the infusion is complete. The approximate total infusion duration is 4 hours.

See Table 1 for the rate of infusion at each step, expressed as mL/hour based on the recommended infusion volume by patient weight.

Do not infuse POMBILITI in the same intravenous line with other products.

Table 1. Recommended POMBILITI Infusion Volumes and Rates by Patient Weight

Patient Weight Range | Total Infusion Volume | Step 1 1 mg/kg/hour | Step 2 3 mg/kg/hour | Step 3 5 mg/kg/hour | Step 4 7 mg/kg/hour
Patient Weight Range | Total Infusion Volume | Infusion Rate in mL/hour
40–50 kg | 250 mL | 13 | 38 | 63 | 88
50.1–60 kg | 300 mL | 15 | 45 | 75 | 105
60.1-100 kg | 500 mL | 25 | 75 | 125 | 175
100.1–120 kg | 600 mL | 30 | 90 | 150 | 210
120.1–140 kg | 700 mL | 35 | 105 | 175 | 245

3 DOSAGE FORMS AND STRENGTHS

For injection: 105 mg of cipaglucosidase alfa-atga as a white to slightly yellowish lyophilized powder with a cake-like appearance in a single-dose vial for reconstitution

4 CONTRAINDICATIONS

POMBILITI in combination with Opfolda is contraindicated in pregnancy [see Warnings and Precautions (5.4) and Use in Specific Populations (8.1)].

5 WARNINGS AND PRECAUTIONS

5.1 Hypersensitivity Reactions Including Anaphylaxis

Life-threatening hypersensitivity reactions, including anaphylaxis, have been reported in POMBILITI-treated patients. In clinical trials, 43 (27%) POMBILITI-treated patients experienced hypersensitivity reactions, including 4 (3%) patients who reported severe hypersensitivity reactions and 4 (3%) additional patients who experienced anaphylaxis (fulfilling at least one of the Sampson criteria). Three of the 4 (2%) patients experiencing anaphylaxis discontinued from the trial [see Clinical Studies (14)]. Two of the 4 patients who experienced anaphylaxis developed high anti-cipaglucosidase alfa-atga antibody titers [see Clinical Pharmacology (12.6)]. Anaphylaxis signs and symptoms included dyspnea, rash, hypotension, bronchospasm, edema, pharyngeal edema, and tongue swelling. Symptoms of severe hypersensitivity reactions included urticaria, pruritus, and flushing.

Prior to POMBILITI administration, consider pretreating with antihistamines, antipyretics, and/or corticosteroids. Appropriate medical support measures, including cardiopulmonary resuscitation equipment, should be readily available during POMBILITI administration.

- If a severe hypersensitivity reaction (e.g., anaphylaxis) occurs, POMBILITI should be discontinued immediately, and appropriate medical treatment should be initiated. The risks and benefits of readministering POMBILITI following severe hypersensitivity reaction (including anaphylaxis) should be considered. Patients may be rechallenged using slower infusion rates. In patients with severe hypersensitivity reaction, desensitization measures to POMBILITI may be considered. If the decision is made to readminister POMBILITI, ensure the patient tolerates the infusion. If the patient tolerates the infusion, the dosage (dose and/or the rate) may be increased to reach the approved recommended dosage.
- If a mild or moderate hypersensitivity reaction occurs, the infusion rate may be slowed or temporarily stopped [see Dosage and Administration (2.3)].

5.2 Infusion-Associated Reactions

In clinical trials, IARs were reported to occur at any time during and/or within a few hours after the POMBILITI infusion and were more likely to occur with higher infusion rates. IARs were reported in 48 (32%) POMBILITI-treated patients in clinical trials. In these trials, 4 (3%) POMBILITI-treated patients reported 11 severe IARs including symptoms of pharyngeal edema, anaphylactic reaction, urticaria, pruritus, chills, dyspnea, and flushing. The majority of IARs were assessed as mild to moderate. IARs that led to treatment discontinuation were urticaria, anaphylactic reaction, chills, and hypotension.

Antihistamines, antipyretics, and/or corticosteroids can be given prior to POMBILITI administration to reduce the risk of infusion-associated reactions (IARs). However, IARs may still occur in patients after receiving pretreatment.

- If severe IARs occur, immediately discontinue the POMBILITI infusion, initiate appropriate medical treatment, and assess the benefits and risks of readministering POMBILITI following severe IARs. Patients may be rechallenged using slower infusion rates. Once a patient tolerates the infusion, the infusion rate may be increased to reach the recommended infusion rate.
- If mild or moderate IARs occur regardless of pretreatment, decreasing the infusion rate or temporarily stopping the infusion may ameliorate the symptoms [see Dosage and Administration (2.3)].

Patients with an acute underlying illness at the time of POMBILITI infusion may be at greater risk for IARs. Patients with advanced Pompe disease may have compromised cardiac and respiratory function, which may predispose them to a higher risk of severe complications from IARs.

5.3 Risk of Acute Cardiorespiratory Failure in Susceptible Patients

Patients susceptible to fluid volume overload, or those with acute underlying respiratory illness or compromised cardiac or respiratory function for whom fluid restriction is indicated may be at risk of serious exacerbation of their cardiac or respiratory status during the POMBILITI infusion. More frequent monitoring of vitals should be performed during POMBILITI infusion in these patients. Some patients may require prolonged observation times.

5.4 Embryo-Fetal Toxicity

Based on findings from animal reproduction studies, POMBILITI in combination with Opfolda may cause embryo-fetal harm when administered to a pregnant female and is contraindicated during pregnancy. In a rabbit embryo-fetal development study, great vessel and cardiac malformations were increased in offspring of pregnant rabbits treated with cipaglucosidase alfa‑atga in combination with oral miglustat at 16‑fold and 3‑fold, respectively, the maximum recommended human dose (MRHD) based on plasma AUC exposure.

Verify the pregnancy status in females of reproductive potential prior to initiating treatment with POMBILITI in combination with Opfolda. Advise females of reproductive potential to use effective contraception during treatment with POMBILITI in combination with Opfolda and for at least 60 days after the last dose [see Use in Specific Populations (8.1, 8.3)].

5.5 Risks Associated with Opfolda

POMBILITI must be administered in combination with Opfolda. Refer to the Opfolda Prescribing Information for a description of additional risks for Opfolda including, but not limited to, the warnings and precautions for Opfolda.

6 ADVERSE REACTIONS

The following clinically significant adverse reactions are described elsewhere in the labeling:

- Hypersensitivity Reactions Including Anaphylaxis [see Warnings and Precautions (5.1)]
- Infusion-Associated Reactions [see Warnings and Precautions (5.2)]

6.1 Clinical Trials Experience

Because clinical trials are conducted under widely varying conditions, adverse reaction rates observed in the clinical trials of a drug cannot be directly compared to rates in the clinical trials of another drug and may not reflect the rates observed in practice.

Adverse Reactions from the Pooled Clinical Trials Including Trial 1

The pooled safety analysis from 3 clinical trials included 151 adult patients with late-onset Pompe disease (LOPD) treated with POMBILITI in combination with Opfolda including:

- 85 patients in the randomized, double-blind, active-controlled trial in adults (Trial 1) [see Clinical Studies (14)],
- 37 patients in the open-label extension trial where patients switched from a non‑U.S.‑approved alglucosidase alfa product [see Clinical Studies (14)] to POMBILITI in combination with Opfolda,
- 29 patients in an open-label trial.

The total median duration of exposure in these trials was 21 months, with 120 patients having at least 12 months exposure to POMBILITI in combination with Opfolda. In these trials, 78% (n=117) of the patients received previous ERT (ERT‑experienced) with a mean treatment duration of 7.7 years.

In these trials, serious adverse reactions reported in 2 or more patients treated with POMBILITI in combination with Opfolda were anaphylaxis and urticaria. A total of 5 patients treated with POMBILITI in combination with Opfolda in these trials permanently discontinued POMBILITI due to adverse reactions, including 4 of these patients who discontinued the treatment because of a serious adverse reaction.

The most common adverse reactions (≥5%) reported in the pooled safety population of patients treated with POMBILITI in combination with Opfolda in the 3 clinical trials were headache, diarrhea, fatigue, nausea, abdominal pain and pyrexia.

In these trials, IARs were reported in 48 (32%) patients treated with POMBILITI in combination with Opfolda. IARs reported in more than 1 patient included headache, myalgia, diarrhea, nausea, fatigue, muscle spasms, pyrexia, dizziness, cough, chills, rash, vomiting, dyspnea, pain, abdominal distension, tachycardia, urticaria, flatulence, pruritus, abdominal pain, chest discomfort, flushing, hyperhidrosis, dysgeusia, hypotension, and hypertension [see Warnings and Precautions (5.2)].

Adverse Reactions from Trial 1

Trial 1 (a randomized, double‑blind, active‑controlled trial) included 123 adult patients with LOPD who were randomized in a 2:1 ratio to receive treatment with POMBILITI in combination with Opfolda or a non-U.S.-approved alglucosidase alfa product with placebo [see Clinical Studies (14)].

The duration of exposure was similar for both treatment groups (overall mean exposure of 12 months). Most patients (77%) were ERT‑experienced, and a majority of patients in both treatment groups had >5 years of prior treatment with ERT (69% and 63% of patients in the POMBILITI in combination with Opfolda group and the non-U.S.-approved alglucosidase alfa product with placebo group, respectively).

The most common adverse reactions (≥5%) reported in the patients who received POMBILITI in combination with Opfolda in Trial 1 were headache and diarrhea.

Table 2 summarizes frequent adverse reactions that occurred in patients treated with POMBILITI in combination with Opfolda in Trial 1. Trial 1 was not designed to demonstrate a statistically significant difference in the incidence of adverse reactions in the POMBILITI in combination with Opfolda and the non-U.S.-approved alglucosidase alfa product with placebo groups.

Table 2. Adverse Reactions that Occurred in Adults with LOPD at an Incidence of ≥2% in Trial 1

Adverse Reaction | POMBILITI in Combination with Opfolda (n=85) N (%) | A Non-U.S.-Approved Alglucosidase alfa Product with Placebo (n=38) N (%)
Headache∗ | 7 (8.2) | 3 (7.9)
Diarrhea | 5 (5.9) | 2 (5.3)
Dizziness | 4 (4.7) | 2 (5.3)
Dyspnea | 3 (3.5) | 0
Abdominal distention | 3 (3.5) | 2 (5.3)
Pyrexia | 3 (3.5) | 1 (2.6)
Rash† | 3 (3.5) | 0
Abdominal pain‡ | 2 (2.4) | 4 (10.5)
Nausea | 2 (2.4) | 5 (13.2)
Chills | 2 (2.4) | 0
Dysgeusia | 2 (2.4) | 0
Flushing | 2 (2.4) | 0
Muscle spasms | 2 (2.4) | 0
Pruritus | 2 (2.4) | 2 (5.3)
Tachycardia§ | 2 (2.4) | 0
Urticaria¶ | 2 (2.4) | 0
LOPD: late-onset Pompe disease
∗ Headache included migraine and migraine with aura.
† Rash included erythematous rash and macular rash.
‡ Abdominal pain included upper and lower abdominal pain.
§ Tachycardia included sinus tachycardia.
¶ Urticaria included mechanical urticaria and urticarial rash.

Additional adverse reactions reported in at least 2% of patients treated with POMBILITI in combination with Opfolda across the 3 clinical trials include: myalgia, arthralgia, increased blood pressure, pain, tremor, dyspepsia, asthenia, constipation, infusion site swelling, flank pain, malaise, paresthesia, somnolence, and decreased platelet count.

Immunogenicity: Anti-Drug Antibody-Associated Adverse Reactions in Trial 1

Anaphylaxis or serious infusion-associated reactions (IARs) occurred in 1 (1.5%) POMBILITI‑treated patient (who previously received U.S.-approved alglucosidase alfa or a non-U.S.-approved alglucosidase alfa product) who had peak anti-cipaglucosidase alfa-atga antibody titer of 6,553,600 during the 52-week treatment period [see Clinical Pharmacology (12.6)].

8 USE IN SPECIFIC POPULATIONS

8.1 Pregnancy

Risk Summary

Based on findings from animal reproduction studies, POMBILITI in combination with Opfolda may cause embryo-fetal harm when administered to a pregnant female and is contraindicated during pregnancy. In a rabbit embryo-fetal development study, great vessel and cardiac malformations were increased in offspring of pregnant rabbits treated with cipaglucosidase alfa-atga in combination with miglustat at 16-fold and 3-fold, respectively, the MRHD of POMBILITI and Opfolda based on plasma AUC exposure. A No Observed Adverse Effect Level (NOAEL) was not identified for the combination. In a pre- and post-natal development study in rats, increases in pup mortality were seen following maternal treatment with cipaglucosidase alfa-atga (400 mg/kg) in combination with miglustat, or with cipaglucosidase alfa-atga (400 mg/kg) alone. The NOAEL for cipaglucosidase alfa-atga alone is 150 mg/kg (5-fold the POMBILITI MRHD margin). A NOAEL for the combination was not identified. Margins at the lowest observed adverse effect level (LOAEL), relative to exposures at the MRHD of POMBILITI and Opfolda were 20-fold and 4-fold, respectively, based on plasma AUC exposure (see Data).

There are no available human data on POMBILITI in combination with Opfolda use in pregnant females to evaluate for a drug-associated risk of major birth defects, miscarriage, or other adverse maternal or fetal outcomes.

Data

Animal Data

Reproductive toxicity studies of cipaglucosidase alfa-atga in rats and rabbits included pretreatment with diphenhydramine (DPH) to prevent or minimize hypersensitivity reactions.

In a rabbit embryo-fetal development study, cipaglucosidase alfa-atga (30, 70, or 175 mg/kg) was administered intravenously every other day to pregnant females during organogenesis (Gestation Day [GD] 7 through GD 19). Additional experimental groups received 25 mg/kg oral miglustat alone, or in combination with intravenous cipaglucosidase alfa-atga 175 mg/kg, with the same dosing frequency during organogenesis. Clusters of great vessel and cardiac malformations were increased in offspring of pregnant rabbits treated with the combination of cipaglucosidase alfa-atga and miglustat at 16-fold and 3-fold the MRHD of POMBILITI and Opfolda, respectively, based on plasma AUC exposure. A NOAEL for the combination was not identified. One fetus treated with cipaglucosidase alfa-atga alone (175 mg/kg) and one fetus treated with miglustat alone (25 mg/kg), each showed a similar cluster of these great vessel and cardiac malformations.

In a rat embryo-fetal development study, cipaglucosidase alfa-atga (75, 150, or 400 mg/kg) was administered intravenously every other day to pregnant rats during organogenesis (GD 6 through GD 18). Additional experimental groups received 60 mg/kg oral miglustat alone, or in combination with intravenous cipaglucosidase alfa-atga 400 mg/kg, with the same dosing frequency during organogenesis. No evidence of adverse effects was noted in pregnant rats or their offspring in any experimental group. The margin at the NOAEL for cipaglucosidase alfa‑atga (400 mg/kg) was 20-fold the POMBILITI MRHD based on plasma AUC exposure. The margin at the NOAEL for miglustat (60 mg/kg) was 4-fold the Opfolda MRHD based on plasma AUC exposure.

In a pre-and post-natal development study in rats, cipaglucosidase alfa-atga (75, 150, or 400 mg/kg) was administered intravenously every other day to pregnant females from GD 6 through GD 18, and from Lactation Day (LD) 1 through LD 19. Additional experimental groups received 60 mg/kg oral miglustat alone, or in combination with intravenous cipaglucosidase alfa‑atga 400 mg/kg, with the same dosing frequency during pregnancy and lactation. Maternal and pup mortality were increased with the combination, and pup mortality was also increased with cipaglucosidase alfa-atga 400 mg/kg alone. The NOAEL for cipaglucosidase alfa-atga alone is 150 mg/kg (5-fold the POMBILITI MRHD margin). A NOAEL was not identified for the combination, for which LOAEL margins at the MRHD of POMBILITI and Opfolda were 20-fold and 4-fold, respectively, based on plasma AUC exposure.

8.2 Lactation

Risk Summary

There are no data on the presence of cipaglucosidase alfa-atga, alone or in combination with miglustat, in human milk, the effects on the breastfed infant, or the effects on milk production. Cipaglucosidase alfa‑atga is present in animal milk (see Data). When a drug is present in animal milk, it is likely that the drug will be present in human milk. Based on findings in animal studies, the use of POMBILITI in combination with Opfolda may lead to serious adverse reactions in breastfed infants. Advise females that breastfeeding is not recommended while on treatment with POMBILITI in combination with Opfolda.

Data

Evaluation of milk in rats from the pre- and post-natal development study of cipaglucosidase alfa atga in combination with miglustat (400 mg/kg and 60 mg/kg, respectively) showed excretion of cipaglucosidase alfa-atga and secretion of miglustat in rat milk. In this study, the ratio of cipaglucosidase alfa-atga exposure in rat milk to cipaglucosidase alfa-atga exposure in rat plasma was <4%, and the ratio of miglustat exposure in rat milk to the miglustat exposure in rat plasma was 1.7.
The concentration of drug in animal milk does not necessarily predict the concentration of drug in human milk.

8.3 Females and Males of Reproductive Potential

POMBILITI in combination with Opfolda may cause embryo-fetal harm when administered to a pregnant female [see Use in Specific Populations (8.1)].

Pregnancy Testing

Verify the pregnancy status in females of reproductive potential prior to initiating treatment with POMBILITI in combination with Opfolda.

Contraception

Females

Advise females of reproductive potential to use effective contraception during treatment with POMBILITI in combination with Opfolda and for at least 60 days after the last dose.

Infertility

Females

Based on preimplantation loss observed in female rats treated with intravenous cipaglucosidase alfa-atga (400 mg/kg) in combination with oral miglustat (60 mg/kg) every other day for 14 days prior to mating, and continuing through GD 7, POMBILITI in combination with Opfolda may impair human female fertility. A NOAEL for the combination was not identified. The LOAEL margins are 27-fold and 4-fold the MRHD for POMBILITI and Opfolda, respectively. It is not known whether this preimplantation loss in female rats would be sustained if dosing with the combination were discontinued prior to mating [see Nonclinical Toxicology (13.1)].

Males

Based on reversible increases in preimplantation loss in male rats treated with the combination every other day for 28 days prior to mating, POMBILITI in combination with Opfolda may impair human male fertility. A NOAEL for the combination was not identified. The LOAEL margins are 27-fold and 4-fold the MRHD for POMBILITI and Opfolda, respectively [see Nonclinical Toxicology (13.1)].

For additional information about male fertility with the use of Opfolda, see the Opfolda Prescribing Information.

8.4 Pediatric Use

Safety and effectiveness of POMBILITI in combination with Opfolda have not been established in pediatric patients with late-onset Pompe disease.

8.5 Geriatric Use

Of the total number of patients treated with POMBILITI in combination with Opfolda in clinical trials for LOPD, 17 (11%) were 65 to 74 years of age, and none were 75 years of age and older [see Clinical Studies (14)].

Clinical trials of POMBILITI in combination with Opfolda did not include sufficient numbers of patients 65 years of age and older to determine whether they respond differently from younger adult patients.

11 DESCRIPTION

Cipaglucosidase alfa-atga is a hydrolytic lysosomal glycogen‑specific recombinant human α‑glucosidase (rhGAA) enzyme derived from a Chinese Hamster Ovary (CHO) cell line using perfusion methodology, resulting in cellularly (CHO)‑derived N‑glycans. Cipaglucosidase alfa‑atga is a glycoprotein with 1.3 mols of bis‑mannose‑6‑phosphate (bis‑M6P) per mol of enzyme. Cipaglucosidase alfa-atga has a molecular weight of approximately 110 kDa.

POMBILITI (cipaglucosidase alfa-atga) for injection is a sterile, white to slightly yellowish lyophilized powder with a cake-like appearance for intravenous use after reconstitution and dilution. Each single-dose vial contains 105 mg of cipaglucosidase alfa-atga and the inactive ingredients citric acid monohydrate (4.57 mg), mannitol (140 mg), polysorbate 80 (3.5 mg), and sodium citrate (39 mg). After reconstitution with Sterile Water for Injection, USP, the resultant concentration is 15 mg/mL with a pH of between 5.7 to 6.3.

12 CLINICAL PHARMACOLOGY

12.1 Mechanism of Action

Pompe disease (also known as glycogen storage disease type II, acid maltase deficiency, and glycogenosis type II) is an inherited disorder of glycogen metabolism caused by a deficiency of lysosomal acid alpha‑glucosidase (GAA) that degrades glycogen to glucose in the lysosome. GAA deficiency results in intra-lysosomal accumulation of glycogen in various tissues.

Cipaglucosidase alfa-atga provides an exogenous source of GAA. The bis-M6P on cipaglucosidase alfa-atga mediates binding to M6P receptors on the cell surface with high affinity. After binding, it is internalized and transported into lysosomes where it undergoes proteolytic cleavage and N‑glycans trimming which are both required to yield the most mature and active form of GAA. Cipaglucosidase alfa-atga then exerts enzymatic activity in cleaving glycogen.

Miglustat binds with, stabilizes, and reduces inactivation of cipaglucosidase alfa-atga in the blood after infusion.

12.2 Pharmacodynamics

In patients with LOPD, excess of glycogen is degraded to hexose tetrasaccharide (Hex4) which is then excreted in urine. The urinary Hex4 assay measures its major component, glucose tetrasaccharide (Glc4). Treatment with POMBILITI in combination with Opfolda resulted in reductions of urinary Glc4 concentrations (normalized by urine creatinine and reported as mmol Glc4/mol creatinine) in adult patients with LOPD.

In ERT‑experienced patients in Trial 1 [see Clinical Studies (14)], the baseline mean urinary Glc4 concentration was 4.6 mmol/mol and 7.2 mmol/mol in the POMBILITI in combination with Opfolda and the non-U.S.-approved alglucosidase alfa product with placebo groups, respectively. The mean percentage (SD) change in urinary Glc4 concentration from baseline to Week 52 was ‑29% (32) and +20% (32) in the POMBILITI in combination with Opfolda and the non-U.S.-approved alglucosidase alfa product with placebo groups, respectively.

12.3 Pharmacokinetics

The maximum plasma concentration (Cmax) and area under the plasma concentration-time curve (AUC) of cipaglucosidase alfa-atga following administration with 20 mg/kg of cipaglucosidase alfa-atga in combination with a single oral dose of 260 mg of Opfolda in adult patients with LOPD are summarized in Table 3.

Table 3. Geometric Mean (CV%) Pharmacokinetic Parameters of Cipaglucosidase alfa‑atga in ERT‑experienced Adult Patients with LOPD

PK Parameter | Cipaglucosidase alfa-atga 20 mg/kg in Combination with Opfolda 260 mg | Cipaglucosidase alfa-atga 20 mg/kg†
Cmax (mcg/mL) | 345 (18.5) | 325 (13.5)
AUC0-inf (mcg*h/mL) | 1812 (20.8) | 1410 (15.9)
CV: coefficient of variation; ERT: enzyme replacement therapy; LOPD: late-onset Pompe disease; PK: pharmacokinetic parameters; Cmax: maximum plasma concentration; AUC: plasma concentration-time curve
† POMBILITI in combination with Opfolda is not approved for use without Opfolda [see Indications and Usage (1)].

Distribution

The volume of distribution of cipaglucosidase alfa-atga ranged from 2.0 to 4.7 L.

Elimination

When cipaglucosidase alfa-atga was administered with Opfolda, the mean total body clearance (CL) of cipaglucosidase alfa-atga was 0.8 L/hour and the mean half-life of cipaglucosidase alfa-atga was 2.1 hours in ERT‑experienced patients.

Metabolism

The metabolic pathway of cipaglucosidase alfa-atga has not been characterized. Cipaglucosidase alfa-atga is expected to be metabolized into small peptides and amino acid via catabolic pathways.

Specific Populations

Age (18 to 74 years) and sex did not have clinically meaningful effects on the pharmacokinetics of cipaglucosidase alfa-atga.

12.6 Immunogenicity

The observed incidence of antidrug antibodies is highly dependent on the sensitivity and specificity of the assay. Differences in assay methods preclude meaningful comparisons of the incidence of antidrug antibodies (ADA) in the trials described below with the incidence of antidrug antibodies in other trials, including those of cipaglucosidase alfa-atga or of other cipaglucosidase alfa products.

Table 4 presents the incidence of ADA and neutralizing antibodies against cipaglucosidase alfa-atga in adult patients with LOPD treated with POMBILITI in combination with Opfolda (who previously received U.S.-approved alglucosidase alfa or a non-U.S.-approved alglucosidase alfa product) during the 52-week treatment period in Trial 1 [see Clinical Studies (14)].

Antibodies against cipaglucosidase alfa-atga (anti-cipaglucosidase alfa-atga antibodies) were cross-reactive to alglucosidase alfa.

Patients who had an IAR post‑treatment were tested for anti-cipaglucosidase alfa-atga IgE antibodies after the occurrence of the IAR. For ERT‑experienced patients, 25% of POMBILITI‑treated patients had IARs, with 1 patient having positive results for anti‑cipaglucosidase alfa-atga IgE antibodies [see Adverse Reactions (6.1)]. Overall, there was no clear trend in IAR occurrence with the development of anti-cipaglucosidase alfa-atga IgE antibodies.

There was no identified clinically significant effect of ADA on pharmacokinetics or pharmacodynamics of POMBILITI in combination with Opfolda over the treatment duration of 52 weeks. Because of the small number of patients with negative ADA, the effect of ADA on the effectiveness of POMBILITI in combination with Opfolda is unknown.

Table 4. Incidence of Anti-Cipaglucosidase alfa-atga IgG Antibodies in ERT-experienced POMBILITI-treated Adult Patients with LOPD (Trial 1)*

Antidrug Antibodies | ERT-experienced Patients¶ (N=65)
ADA at Baseline | n=55 (85%)
ADA at Week 52 | n=58 (89%)
Inhibition of enzyme activity† | n=26 (40%)
Inhibition of enzyme activity‡ | n=24 (37%)
Inhibition of CI-MPR binding§ | n=53 (82%)
ERT: enzyme replacement therapy; LOPD: late-onset Pompe disease
∗ In this table, ADAs (antidrug antibodies) are anti-cipaglucosidase alfa-atga IgG antibodies, and neutralizing IgG antibodies are against cipaglucosidase alfa-atga.
† Enzyme activity measured as 4-methylumbelliferone-α-D-glucopyranoside (4-MU-α-Glc) hydrolysis
‡ Enzyme activity measured as glycogen hydrolysis
§ Inhibition of cation independent mannose-6-phosphate receptor (CI-MPR) binding
¶ ERT‑experienced patients received U.S.-approved alglucosidase alfa or a non-U.S.-approved alglucosidase alfa product before they received POMBILITI.

13 NONCLINICAL TOXICOLOGY

13.1 Carcinogenesis, Mutagenesis, Impairment of Fertility

Carcinogenesis

Studies in animals to evaluate the carcinogenic potential of cipaglucosidase alfa-atga have not been conducted. For information on an evaluation of carcinogenicity of miglustat in animals, see the Opfolda Prescribing Information.

Mutagenesis

Studies to evaluate the mutagenic or genotoxic potential of cipaglucosidase alfa-atga have not been conducted. For information regarding the mutagenesis of miglustat, see the Opfolda Prescribing Information.

Impairment of Fertility

In a fertility study in rats, cipaglucosidase alfa-atga (75, 150, or 400 mg/kg) was administered intravenously to male and female rats every other day. Dosing in males was initiated 28 days prior to cohabitation with untreated females. Dosing in females was initiated 14 days prior to cohabitation with untreated males and continued through GD 7. Additional experimental groups received 60 mg/kg oral miglustat alone, or in combination with intravenous cipaglucosidase alfa‑atga 400 mg/kg, with the same frequency over the same pre‑mating interval (males) or pre-mating and pregnancy interval (females).

There was no effect on male or female rat fertility in any experimental group. Treatment of male rats with the combination was associated with increased preimplantation loss that was reversible. Treatment of female rats with the combination, or with miglustat alone, resulted in preimplantation loss; whether this would be reversible if treatment were discontinued prior to cohabitation is unknown. NOAELs were not identified for the combination in either male or female rats. The LOAEL margins for these doses represent 27-fold and 4-fold the MRHD of POMBILITI and Opfolda, respectively, based on plasma AUC exposure.

13.2 Animal Toxicology and/or Pharmacology

For additional animal toxicology findings for miglustat, see the Opfolda Prescribing Information.

14 CLINICAL STUDIES

Trial 1 was a randomized, double‑blind, active‑controlled, international, multi‑center clinical trial (NCT#03729362) in patients ≥18 years old diagnosed with LOPD. Patients were randomized 2:1 to receive POMBILITI (20 mg/kg by intravenous infusion) in combination with Opfolda (260 mg orally for those ≥50 kg or 195 mg orally for those ≥40 kg to <50 kg) or a non-U.S.-approved alglucosidase alfa product with placebo every other week for 52 weeks. The efficacy population included a total of 123 patients of whom 95 (77%) had received prior treatment with U.S.-approved alglucosidase alfa or a non-U.S.-approved alglucosidase alfa product (ERT‑experienced) and 28 (23%) were ERT‑naïve. More than two thirds (n=64, 67%) of ERT‑experienced patients had been on ERT treatment for more than 5 years prior to entering Trial 1 (mean of 7.4 years).

Demographics, baseline sitting forced vital capacity (FVC) (% predicted), and 6-minute walk distance (6MWD) were generally similar between the 2 treatment groups (see Table 5 for baseline sitting FVC [percent predicted] values). Of the 123 randomized patients, 56 were males, baseline mean age was 47 years old (range from 19 to 74 years old), and mean age at diagnosis was 39 years old (range from 1 to 66). The racial groups for the patients consisted of 104 White (85%), 6 Japanese (5%), 6 Other racial group (5%), 4 Asian (3%), 1 Native Hawaiian or other Pacific Islander (1%), 1 American Indian or Alaska Native (1%), and 1 Black or African American (1%).

Key efficacy endpoints included assessment of sitting FVC (% predicted) and 6MWD (Table 5 and Table 6).

Sitting FVC (Percent‑predicted) at 52 Weeks

Patients treated with POMBILITI in combination with Opfolda showed a mean change in sitting FVC from baseline at Week 52 of -1.1% as compared with patients treated with a non-U.S.-approved alglucosidase alfa product with placebo of -3.3%; the estimated treatment difference was 2.3% (95% CI: 0.02, 4.62).

The ERT‑experienced patients treated with POMBILITI in combination with Opfolda showed a numerically favorable change in sitting FVC from baseline at Week 52 (Table 5 and Figure 2).

Table 5. Summary of Sitting FVC in Adults with LOPD by ERT Status at 52 Weeks in Trial 1

Efficacy Endpoint | ERT-experienced |  | ERT-naïve*
Sitting FVC (% predicted) | POMBILITI in Combination with Opfolda | A Non-U.S.-Approved Alglucosidase alfa Product† with Placebo | POMBILITI in Combination with Opfolda | A Non-U.S.-Approved Alglucosidase alfa Product† with Placebo
Baseline n Mean (SD) Median | n=65 67.9 (19.1) 68.0 | n=30 67.5 (21.0) 69.0 | n=20 80.2 (18.7) 82.3 | n=8 79.6 (21.0) 88.5
Change from baseline at Week 52 n Mean (SD) Median | n=55 0.1 (5.9) 0.5 | n=26 -3.5 (4.7) -2.5 | n=19 -4.7 (6.2) -4.5 | n=7 -2.4 (6.3) -3.0
Change to Week 52 Diff. of means (SE) (95% CI) | 3.5 (1.3) (1.0, 6.0)‡ |  | -1.9 (2.7) (-7.3, 3.6)
FVC: forced vital capacity; LOPD: late-onset Pompe disease; ERT: enzyme replacement therapy; SD: standard deviation; Diff.: difference; SE: standard error; CI: confidence interval
∗ POMBILITI in combination with Opfolda is not approved for use in ERT-naïve patients with LOPD [see Indications and Usage (1)]. The ERT-naïve patient subgroup enrolled too few patients to conclusively interpret the data. For the ERT-naïve group, the treatment difference was estimated using a 2-sample t-test.
† A U.S.-approved alglucosidase alfa product was not used in this clinical trial. Conclusions cannot be drawn from this clinical trial regarding comparative effectiveness between a U.S.-approved alglucosidase alfa product and POMBILITI in combination with Opfolda for the treatment of adult patients with LOPD weighing ≥40 kg and who are not improving on their current ERT.
‡ For the ERT‑experienced group, the treatment difference of the mean was estimated by analysis of covariance which included treatment, gender, baseline FVC, age, weight, and height in the model. Nominal p=0.006. Missing data at Week 52 was imputed using last observed values.

Figure 2. Mean Change (± SE) in Sitting FVC (% predicted) from Baseline to Week 52 in ERT-experienced Adults with LOPD in Trial 1*

SE: standard error; FVC: forced vital capacity; ERT: enzyme replacement therapy; LOPD: late-onset Pompe disease

∗ A U.S.-approved alglucosidase alfa product was not used in this clinical trial. Conclusions cannot be drawn from this clinical trial regarding comparative effectiveness between a U.S.-approved alglucosidase alfa product and POMBILITI in combination with Opfolda for the treatment of adult patients with LOPD weighing ≥40 kg and who are not improving on their current ERT.

6 Minute Walk Distance (6MWD) at 52 Weeks

Patients treated with POMBILITI in combination with Opfolda walked on average 21 meters farther from baseline as compared to those treated with a non-U.S.-approved alglucosidase alfa product with placebo who walked 8 meters farther from baseline; the estimated treatment difference was 14 meters (95% CI: -1, 28).

The ERT‑experienced patients treated with POMBILITI in combination with Opfolda showed a numerically favorable change in 6MWD from baseline at Week 52 (Table 6 and Figure 3).

Table 6. Summary of 6MWD in Adults with LOPD by ERT Status at 52 Weeks in Trial 1

Efficacy Endpoint | ERT‑experienced |  | ERT‑naïve*
6MWD | POMBILITI in Combination with Opfolda | A Non-U.S.-Approved Alglucosidase alfa Product† with Placebo | POMBILITI in Combination with Opfolda | A Non-U.S.-Approved Alglucosidase alfa Product† with Placebo
Baseline n Mean (SD) Median | n=65 347 (110) 353 | n=30 335 (114) 344 | n=20 394 (112) 375 | n=7 421 (136) 386
Change from baseline at Week 52 n Mean (SD) Median | n=61 16 (39) 10 | n=29 1 (40) -9 | n=20 33 (49) 24 | n=7 38 (29) 34
Change to Week 52 Diff. of means (SE) (95% CI) | 17 (8) (0.2, 33)‡ |  | -5 (20) (-45, 36)
6MWD: 6-minute walk distance; LOPD: late-onset Pompe disease; ERT: enzyme replacement therapy; SD: standard deviation; Diff.: difference; SE: standard error; CI: confidence interval
∗ POMBILITI in combination with Opfolda is not approved for use in ERT‑naïve patients with LOPD [see Indications and Usage (1)]. The ERT-naïve patient subgroup enrolled too few patients to conclusively interpret the data. For the ERT‑naïve group, the treatment difference was estimated using a 2-sample t-test. One ERT‑naïve subject in the control arm was excluded from this table because their change of 355 meters in 6MWD from baseline at Week 52 was a statistical outlier and not considered clinically plausible.
† A U.S.-approved alglucosidase alfa product was not used in this clinical trial. Conclusions cannot be drawn from this clinical trial regarding comparative effectiveness between a U.S.-approved alglucosidase alfa product and POMBILITI in combination with Opfolda for the treatment of adult patients with LOPD weighing ≥40 kg and who are not improving on their current ERT.
‡ For the ERT‑experienced group, the treatment difference of the mean was estimated by nonparametric analysis of covariance which included treatment, gender, baseline 6MWD, age, weight, and height in the model. Nominal p=0.047. Missing data at Week 52 was imputed using last observed values.

Figure 3. Mean Change (± SE) of 6MWD from Baseline to Week 52 in ERT‑experienced Adults with LOPD in Trial 1*

SE: standard error; 6MWD: 6-minute walk distance; ERT: enzyme replacement therapy; LOPD: late-onset Pompe disease

∗ A U.S.-approved alglucosidase alfa product was not used in this clinical trial. Conclusions cannot be drawn from this clinical trial regarding comparative effectiveness between a U.S.-approved alglucosidase alfa product and POMBILITI in combination with Opfolda for the treatment of adult patients with LOPD weighing ≥40 kg and who are not improving on their current ERT.

16 HOW SUPPLIED/STORAGE AND HANDLING

How Supplied

POMBILITI (cipaglucosidase alfa-atga) for injection is supplied as a sterile, white to slightly yellowish lyophilized powder with a cake-like appearance in a single‑dose vial. POMBILITI does not contain any preservatives. See Table 7 for the available POMBILITI packages.

Table 7. POMBILITI Cartons

Carton | NDC
Contains one (1) 105 mg single-dose vial | 71904‑200‑01
Contains ten (10) 105 mg single-dose vials | 71904‑200‑02
Contains twenty-five (25) 105 mg single-dose vials | 71904‑200‑03

Storage and Handling

Store refrigerated at 2℃ to 8℃ (36℉ to 46℉) in the original carton to protect from light. Do not freeze.

For storage of the reconstituted solution and diluted solution [see Dosage and Administration (2.5)].

17 PATIENT COUNSELING INFORMATION

POMBILITI must be administered in combination with Opfolda. Refer to the Opfolda Prescribing Information for Opfolda patient counseling information.

Administration
Advise the patient and caregiver to follow the timeline recommendations for taking Opfolda prior to the intravenous infusion with POMBILITI [see Dosage and Administration (2.2)].

Hypersensitivity Reactions (Including Anaphylaxis) and Infusion-Associated Reactions (IARs)
Advise the patient and caregiver that reactions related to the infusion may occur during and after POMBILITI in combination with Opfolda treatment, including life-threatening hypersensitivity reactions, including anaphylaxis, and IARs. Inform the patient and caregiver of the signs and symptoms of hypersensitivity reactions and IARs and to seek medical care should signs and symptoms occur [see Warnings and Precaution (5.1, 5.2)].

Risk of Acute Cardiorespiratory Failure
Advise the patient and caregiver that a patient with underlying respiratory illness or compromised cardiac or respiratory function may be at risk of acute cardiorespiratory failure from volume overload during POMBILITI infusion and to seek medical care should signs and symptoms occur [see Warnings and Precaution (5.3)].

Embryo-Fetal Toxicity
POMBILITI in combination with Opfolda may cause embryo-fetal harm. Advise a female patient and caregiver to inform their healthcare provider of a known or suspected pregnancy [see Warnings and Precautions (5.4) and Use in Specific Populations (8.1)].

Advise a female of reproductive potential to use effective contraception during treatment with POMBILITI in combination with Opfolda and for at least 60 days after the last dose [see Use in Specific Populations (8.1, 8.3)].

Lactation
Advise a lactating female not to breastfeed during treatment with POMBILITI in combination with Opfolda [see Use in Specific Populations (8.2)].

Infertility
Advise the male or female of reproductive potential that POMBILITI in combination with Opfolda may impair fertility [see Use in Specific Populations (8.3)].

Manufactured by:
Amicus Therapeutics US, LLC
3675 Market Street
Philadelphia, PA 19104

U.S. License No. 2224

POMBILITI and Opfolda are registered trademarks of Amicus Therapeutics, Inc.
For more information, go to pombilitiopfoldahcp.com.